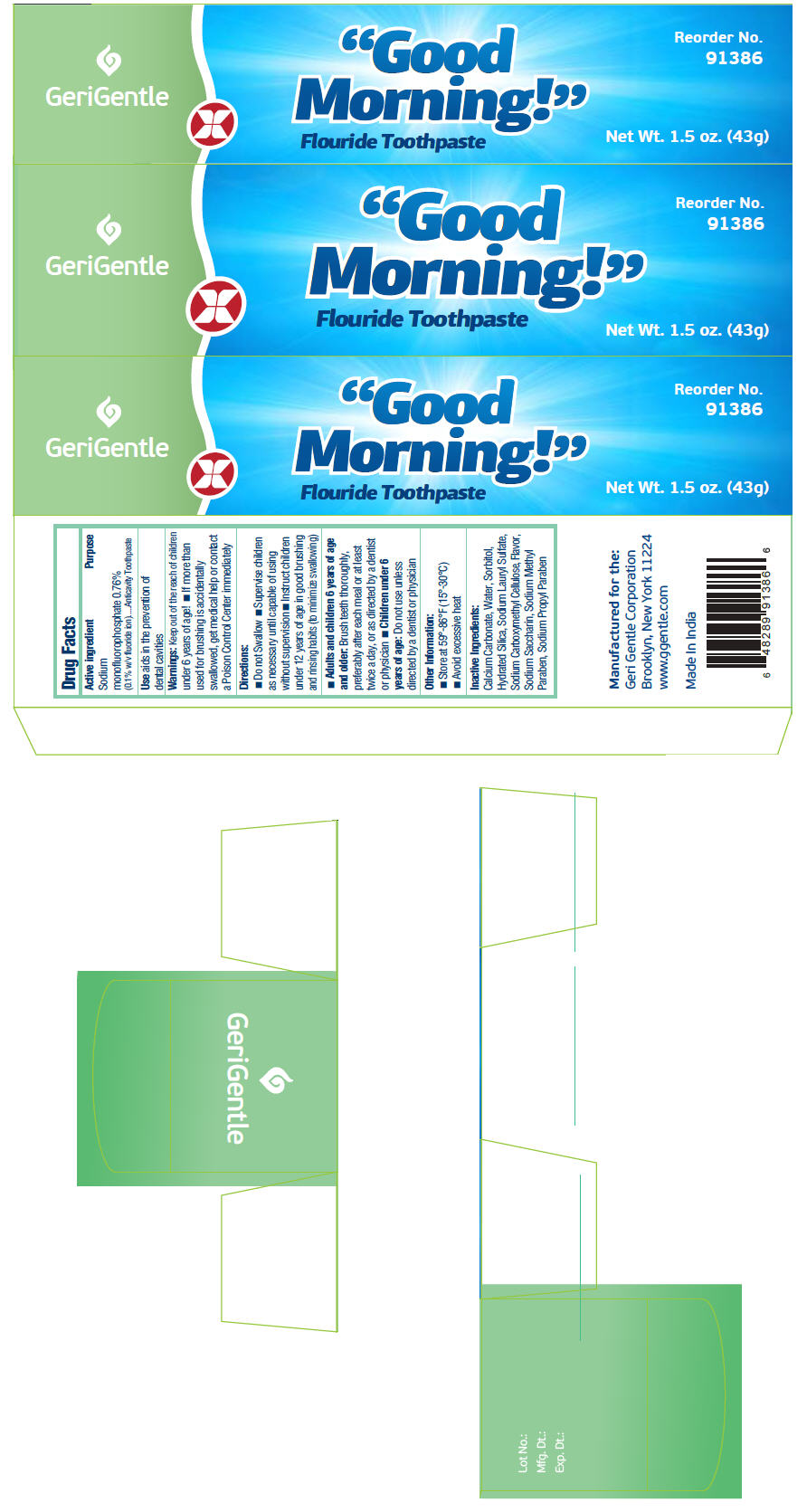 DRUG LABEL: Gerigentle-Good morning
NDC: 69771-107 | Form: PASTE, DENTIFRICE
Manufacturer: Geri-Gentle Corporation
Category: otc | Type: HUMAN OTC DRUG LABEL
Date: 20210831

ACTIVE INGREDIENTS: SODIUM MONOFLUOROPHOSPHATE 0.1 g/100 g
INACTIVE INGREDIENTS: CALCIUM CARBONATE; WATER; SORBITOL; HYDRATED SILICA; SODIUM LAURYL SULFATE; CARBOXYMETHYLCELLULOSE SODIUM, UNSPECIFIED FORM; SACCHARIN SODIUM; METHYLPARABEN SODIUM; PROPYLPARABEN SODIUM

Gerigentle-Good morning

Drug Facts

Active ingredient

Sodium monofluorophosphate 0.76% (0.1% w/v fluoride ion)

Purpose

Anticavity Toothpaste

Use

aids in the prevention of dental cavities

Warnings

KEEP OUT OF REACH OF CHILDREN

Keep out of the reach of children under 6 years of age!

- If more than used for brushing is accidentally swallowed, get medical help or contact a Poison Control Center immediately

Directions

- Do not Swallow
- Supervise children as necessary until capable of using without supervision
- Instruct children under 12 years of age in good brushing and rinsing habits (to minimize swallowing)
- Adults and children 6 years of age and older: Brush teeth thoroughly, preferably after each meal or at least twice a day, or as directed by a dentist or physician
- Children under 6 years of age: Do not use unless directed by a dentist or physician

Other Information

- Store at 59°-86°F (15°-30°C)
- Avoid excessive heat

Inactive Ingredients

Calcium Carbonate, Water, Sorbitol, Hydrated Silica, Sodium Lauryl Sulfate, Sodium Carboxymethyl Cellulose, Flavor, Sodium Saccharin, Sodium Methyl Paraben, Sodium Propyl Paraben

PRINCIPAL DISPLAY PANEL - 43 g Tube Carton

GeriGentle

"Good
Morning!"

Flouride Toothpaste

Reorder No.
91386

Net Wt. 1.5 oz. (43g)